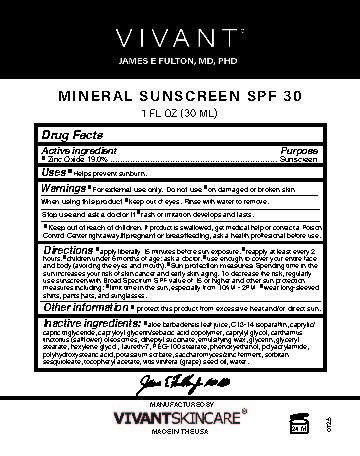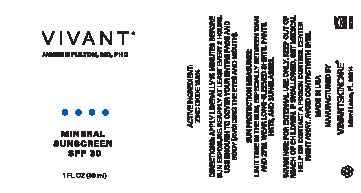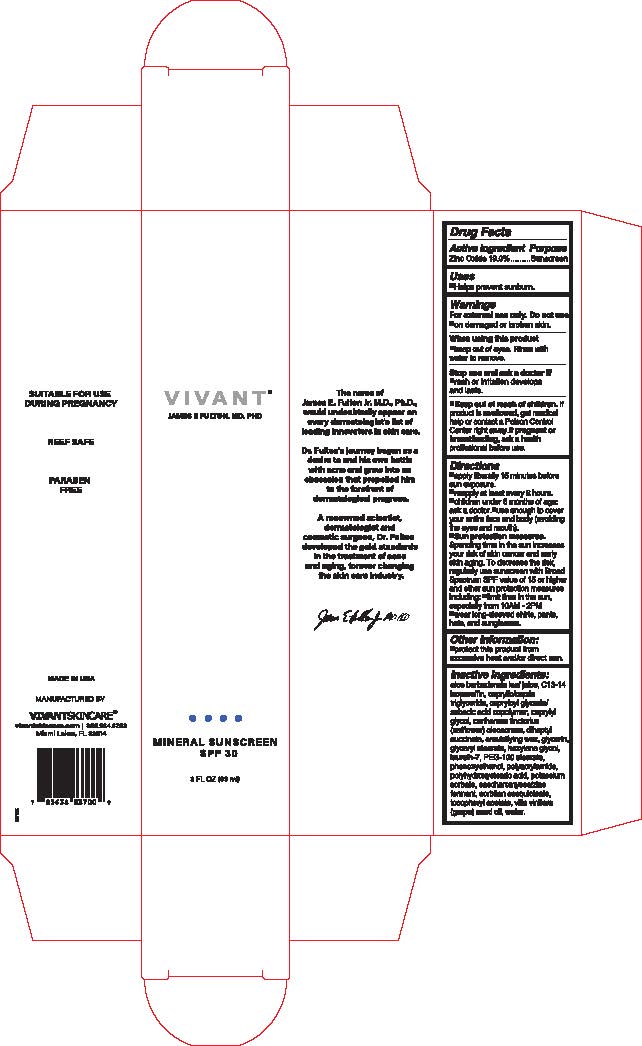 DRUG LABEL: Mineral Suscreen SPF 30
NDC: 63750-038 | Form: CREAM
Manufacturer: Vivant Pharmaceuticals, LLC
Category: otc | Type: HUMAN OTC DRUG LABEL
Date: 20250724

ACTIVE INGREDIENTS: ZINC OXIDE 19 mg/1 g
INACTIVE INGREDIENTS: YEAST, UNSPECIFIED; CETEARYL ALCOHOL; LAURETH-7; GLYCERIN; CAPRYLIC/CAPRIC TRIGLYCERIDE; HEXYLENE GLYCOL; CAPRYLOYL GLYCERIN/SEBACIC ACID COPOLYMER (2000 MPA.S); PEG-100 STEARATE; C13-14 ISOPARAFFIN; PHENOXYETHANOL; POTASSIUM SORBATE; WATER; DIHEPTYL SUCCINATE; GLYCERYL STEARATE; POLYHYDROXYSTEARIC ACID (2300 MW); POLYACRYLAMIDE (10000 MW); ALOE VERA LEAF JUICE; .ALPHA.-TOCOPHEROL ACETATE; CARTHAMUS TINCTORIUS (SAFFLOWER) OLEOSOMES; GRAPE SEED OIL; SORBITAN SESQUIOLEATE; CAPRYLYL GLYCOL; POLYSORBATE 60

Vivant Skincare Sunscreen SPF 30

Active Ingredients

Zinc Oxide 19.0%

Purpose

Sunscreen

Uses

Helps prevent sunburn.

Warnings

For external use only.

Do not use on damaged or broken skin.

.

When using this product

Keep out of eyes. Rinse with water to remove.

Stop use and ask doctor

rash or irritation develops and lasts

Inactive Ingredients:

aloe barbadensis leaf juice, C13-14 isoparaffin, caprylic/capric triglyceride, capryloyl glycerin/sebacic acid copolymer, caprylyl glycol, carthamus tinctorius (safflower) oleosomes, diheptyl succinate, emulsifying wax, glycerin, glyceryl stearate, hexylene glycol, laureth-7, PEG-100 stearate, phenoxyethanol, polyacrylamide, polyhydroxystearic acid, potassium sorbate, saccharomyces/zinc ferment, sorbitan sesquioleate, tocopheryl acetate, vitis vinifera (grape) seed oil, water

Keep out of reach of children. If product is swallowed, get medical help or contact a Poison Control Center right away. If pregnant or breastfeeding, ask a health professional before use.

Directions

Apply liberally 15 minutes before sun exposure. Reapply at least every 2 hours.

Children under 6 months of age: ask a doctor.

Use enough to cover your entire face and body (avoiding the eyes and mouth)

Sun protection measures. Spending time in the sun increases your risk of skin cancer and early skin again. To decrease the risk, regularly use a sunscreen with a Broad Spectrum SPF value of 15 or higher and other sun protection measures including:

limit time in the sun, especially from 10 a.m. – 2 p.m.

wear long-sleeved shirts, pants, hats and sunglasses.

Other Information:

Protect this product from excessive heat and direct sun.